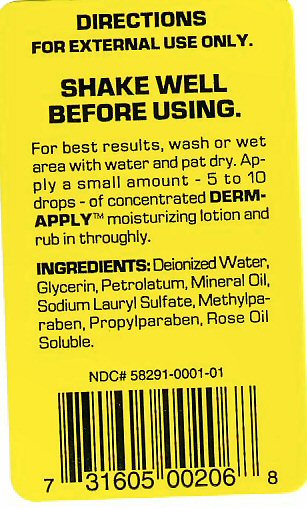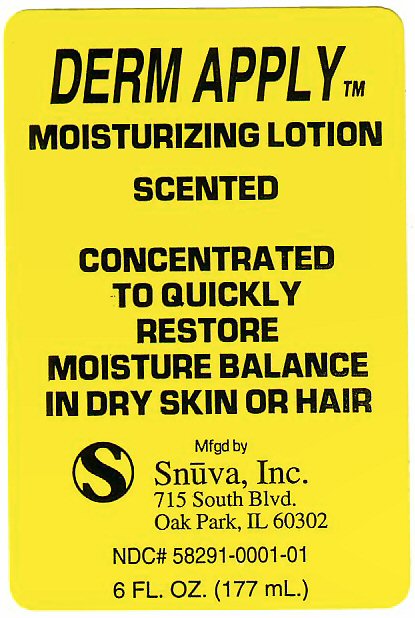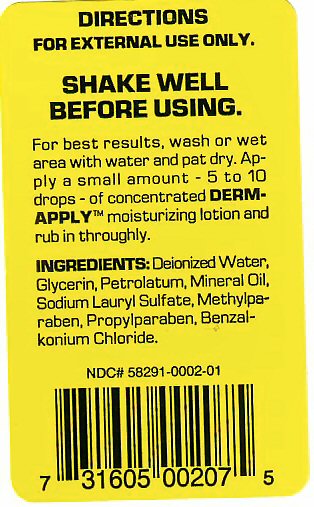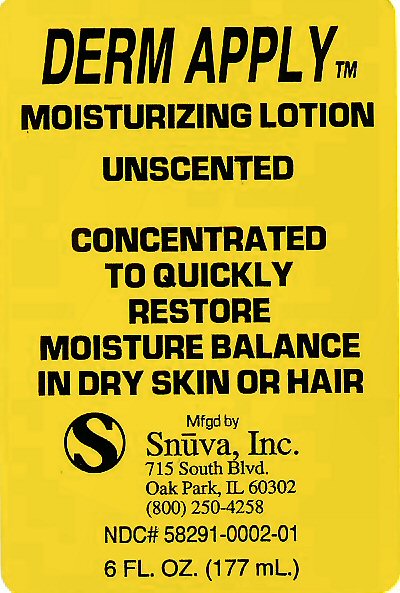 DRUG LABEL: DERM-APPLY
NDC: 58291-0001 | Form: LIQUID
Manufacturer: Snuva, Inc.
Category: otc | Type: HUMAN OTC DRUG LABEL
Date: 20101123

ACTIVE INGREDIENTS: GLYCERIN 30.78 mL/100 mL
INACTIVE INGREDIENTS: WATER; ROSE OIL; PROPYLPARABEN; SODIUM LAURYL SULFATE; MINERAL OIL; PETROLATUM

ACTIVE INGREDIENT

GLYCERIN

INACTIVE INGREDIENTS

DEIONIZED WATER, PETROLATUM, MINERAL OIL, SODIUM LAURYL SULFATE, METHYLPARABEN, PROPYLPARABEN

PURPOSE

RESTORE MOISTURE BALANCE IN DRY SKIN OR HAIR

USE

CONCENTRATED, FOR EXTERNAL USE ONLY

KEEP OUT OF REACH OF CHILDREN

Enter section text here

DIRECTIONS

SHAKE WELL BEFORE USING

FOR BEST RESULTS, WASH OR WET AREA WITH WATER AND PAT DRY. APPLY A SMALL AMOUNT - 5 TO 10 DROPS OF CONCENTRATED DERM-APPLY MOISTURIZING LOTION AND RUB IN THOROUGHLY.

WARNINGS

FOR EXTERNAL USE ONLY. SHAKE WELL BEFORE USING

DERM-APPLY LABEL

DERM-APPLY tm MOISTURIZING LOTION

CONCENTRATED TO QUICKLY RESTORE MOISTURE BALANCE IN DRY SKIN OR HAIR

MANUFACTURED BY SNUVA, INC 715 SOUTH BLVD OAK PARK, IL 60302